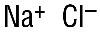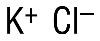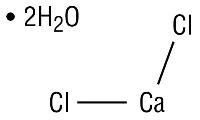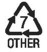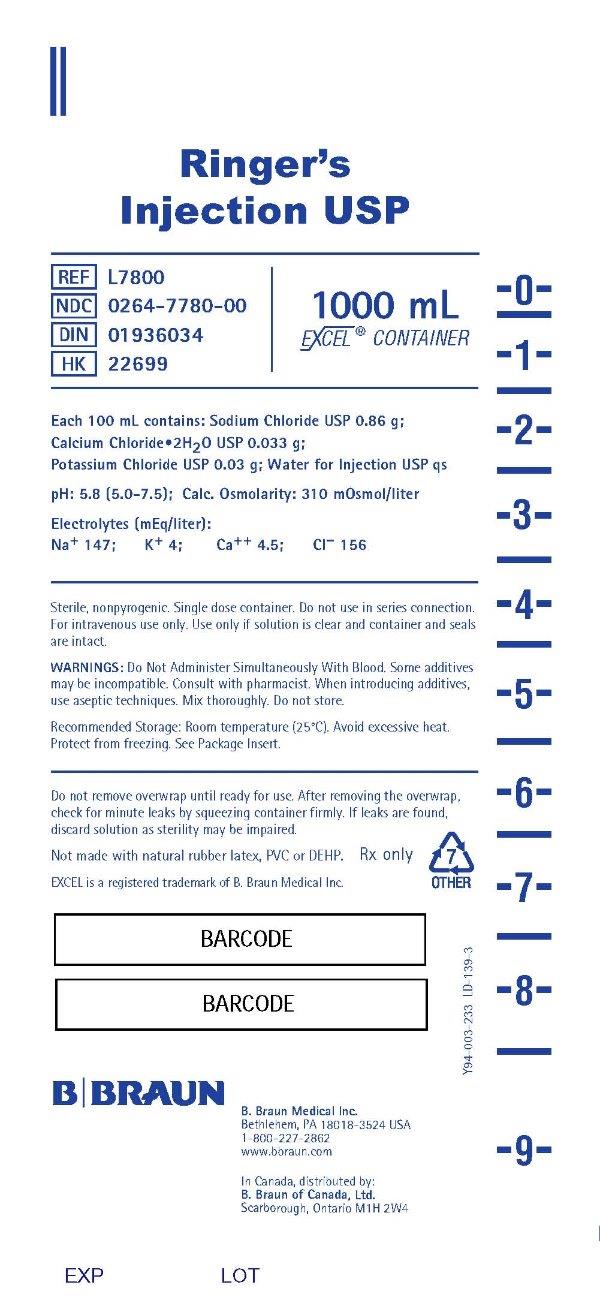 DRUG LABEL: Ringers
NDC: 0264-7780 | Form: INJECTION, SOLUTION
Manufacturer: B. Braun Medical Inc.
Category: prescription | Type: HUMAN PRESCRIPTION DRUG LABEL
Date: 20251105

ACTIVE INGREDIENTS: SODIUM CHLORIDE 0.86 g/100 mL; CALCIUM CHLORIDE 0.033 g/100 mL; POTASSIUM CHLORIDE 0.03 g/100 mL
INACTIVE INGREDIENTS: WATER

HIGHLIGHTS OF PRESCRIBING INFORMATION

These highlights do not include all the information needed to use RINGER’S INJECTION safely and effectively. See full prescribing information for RINGER’S INJECTION.
RINGER’S injection, for intravenous use
Initial U.S. Approval: 1971

RECENT MAJOR CHANGES

Dosage and Administration (2.1, 2.2, 2.3, 2.4) 10/2025
Contraindications (4) 10/2025
Warnings and Precautions (5.1, 5.2, 5.3, 5.4, 5.5, 5.6, 5.7) 10/2025

1 INDICATIONS AND USAGE

Ringer’s Injection is indicated for use as a source of water and electrolytes in adults and pediatric patients. (1)

2 DOSAGE AND ADMINISTRATION

- The recommended dosage and duration are based on the patient’s age, weight, clinical condition, and concomitant therapy. (2.1)
- To reduce the risk of air embolism, adhere to the preparation instructions. (2.2, 5.2)
- Ringer’s Injection is for intravenous use (2.3)
- Do not administer Ringer’s Injection simultaneously with ceftriaxone in neonates (28 days of age or younger) due to serious risks. (2.4)
- See full prescribing information for information dosage considerations, preparation, administration, and drug incompatibilities. (2)

3 DOSAGE FORMS AND STRENGTHS

Injection: Ringer’s Injection USP packaged in single-dose Excel® Container: 1000 mL (3)

4 CONTRAINDICATIONS

- Concomitant treatment with ceftriaxone in neonates (28 days of age or younger). (4)
- Patients with known hypersensitivity to Ringer’s Injection. (4)

5 WARNINGS AND PRECAUTIONS

- Serious Risks with Inappropriate Use with Ceftriaxone: Deaths have occurred in neonates (28 days of age or younger) who received concomitant intravenous calcium-containing solutions with ceftriaxone. In patients older than 28 days, ceftriaxone and Ringer’s Injection may be administered sequentially if the infusion lines are thoroughly flushed between infusions. (4, 5.1, 8.4)
- Air Embolism: Use a non-vented infusion set or close the vent on a vented set and use a dedicated line without any connections. Pressure infusion is not recommended to increase flow rates, but if necessary, remove all air from the bag prior to initiating infusion. (5.2)
- Hypersensitivity Reactions: Stop the Ringer’s Injection infusion immediately if signs or symptoms of a hypersensitivity reaction develop. (5.3)
- Potassium Imbalances, Hyponatremia, Hypercalcemia, Fluid Overload: See Full Prescribing Information for risk management recommendations. (5.4, 5.5, 5.6, 5.7)

6 ADVERSE REACTIONS

Common adverse reactions include infusion site reactions and symptoms of hypersensitivity reactions (e.g., pruritus, dyspnea, urticaria, rash, cough). (6)

To report SUSPECTED ADVERSE REACTIONS, contact B. Braun Medical Inc. at 1-833-425-1464 or FDA at 1-800-FDA-1088 or www.fda.gov/medwatch.

7 DRUG INTERACTIONS

- Drugs that Affect Electrolyte and/or Fluid Balance: Avoid concomitant use. If concomitant use cannot be avoided, closely monitor electrolyte concentrations and fluid balance. (7.1)
- Lithium: Avoid concomitant use. If concomitant use is unavoidable monitor serum lithium concentrations more frequently. (7.2)
- Digoxin: Consider reducing the volume or rate of Ringer’s Injection due to the increased risk of digoxin toxicity with calcium-containing solutions. (7.3)

8 USE IN SPECIFIC POPULATIONS

- Closely monitor plasma electrolyte concentrations in young pediatric patients with immature kidney function. (8.4).
- Geriatric patients are more likely to have decreased renal function. Consider monitoring renal function and starting the infusion at the low end of the dosing range. (8.5)
- Avoid in patients with severe renal impairment. (8.6)

FULL PRESCRIBING INFORMATION

1 INDICATIONS AND USAGE

Ringer’s Injection is indicated for use as a source of water and electrolytes in adults and pediatric patients.

2 DOSAGE AND ADMINISTRATION

2.1 Dosage Considerations

The recommended dosage and duration of Ringer’s Injection is based on the patient’s age, weight, clinical condition, and concomitant therapy. Evaluate the patient’s clinical status and monitor changes in electrolyte concentrations especially during prolonged use of Ringer’s Injection to optimize clinical status.

Fluid administration should be based on calculated maintenance or replacement fluid requirements for each patient.

2.2 Important Preparation Instructions

Visually inspect the Ringer’s Injection solution for particulate matter and discoloration. Do not administer Ringer’s Injection unless the solution is clear and the container seals are intact.

If additives are determined to be compatible with Ringer’s Injection, then using aseptic technique, mix thoroughly; do not store solutions containing additives. After mixing, do not use if there is discoloration or formation of precipitates.

To reduce the risk of air embolism, adhere to the following Ringer’s Injection preparation instructions [see Warnings and Precautions (5.2)]:

- Use a non-vented infusion set or close the vent on a vented set.
- Use a dedicated line without any connections (do not connect flexible containers in series).
- The use of pressure infusion is not recommended as a method to increase flow rates. However, if pressure infusion is required, ensure that any air within the bag is fully evacuated prior to initiation of infusion.
- If using a pumping device to administer Ringer’s Injection, turn off the pump before the container is empty.

Preparation Instructions for EXCEL® Containers

1. Tear overwrap down at notch and remove solution container. Check for minute leaks by squeezing solution container firmly. If leaks are found, discard solution as sterility may be impaired. If supplemental medication is desired, follow directions below before preparing for administration.
2. Inspect each container. Read the label. Ensure solution is the one ordered and is within the expiration date.
3. Invert container and carefully inspect the solution in good light for cloudiness, haze, or particulate matter. Any container which is suspect should not be used.
4. If supplemental medication is desired, follow directions below [see Dosage and Administration (2.3)].

Preparation for Administration

1. Remove plastic protector from sterile set port at bottom of container.
2. Attach administration set according to its accompanying directions.

2.3 Important Administration Instructions

Ringer’s Injection is for intravenous use.

Use immediately after opening the container. Discard the unused portion.

It is recommended that intravenous administration apparatus be replaced at least once every 24 hours.

Some additives may be incompatible [see Dosage and Administration (2.4)].

To Add Medication Before Solution Administration

1. Prepare medication site.
2. Using syringe with 18-22 gauge needle, puncture medication port and inner diaphragm and inject.
3. Squeeze and tap ports while ports are upright and mix solution and medication thoroughly.

To Add Medication During Solution Administration

1. Close clamp on the set.
2. Prepare medication site.
3. Using syringe with 18-22 gauge needle of appropriate length (at least 5/8 inch), puncture resealable medication port and inner diaphragm and inject.
4. Remove container from IV pole and/or turn to an upright position.
5. Evacuate both ports by tapping and squeezing them while container is in the upright position.
6. Mix solution and medication thoroughly.
7. Return container to in use position and continue administration.

2.4 Drug Incompatibilities

Do not administer Ringer’s Injection simultaneously with ceftriaxone in neonates (28 days of age or younger) due to serious risks [see Contraindications (4) and Warnings and Precautions (5.1)]. However, in patients older than 28 days, ceftriaxone and Ringer’s Injection may be administered sequentially if the infusion lines are thoroughly flushed between infusions with a compatible fluid [see Warnings and Precautions (5.1)].

Do not administer Ringer’s Injection simultaneously with citrate anticoagulated/preserved blood through the same administration set because of the likelihood of coagulation precipitated by the calcium content of Ringer’s Injection.

3 DOSAGE FORMS AND STRENGTHS

Injection: Ringer’s Injection USP as a clear, sterile, and nonpyrogenic solution packaged in a single-dose container: 1,000 mL.

4 CONTRAINDICATIONS

Ringer’s Injection is contraindicated in:

- Neonates (28 days of age or younger) who are receiving concomitant treatment with ceftriaxone, even if separate infusion lines are used, due to the risk of fatal ceftriaxone-calcium salt precipitation in the neonate’s bloodstream [see Warnings and Precautions (5.1) and Specific Populations (8.4)].
- Patients with known hypersensitivity to any components of Ringer’s Injection [see Warnings and Precautions (5.3)].

5 WARNINGS AND PRECAUTIONS

5.1 Serious Risk with Concomitant Use with Ceftriaxone

Precipitation of ceftriaxone-calcium can occur when ceftriaxone is mixed with calcium-containing solutions, such as Ringer’s Injection in the same intravenous administration line. Deaths have occurred in neonates (28 days of age or younger) who received concomitant intravenous calcium-containing solutions with ceftriaxone resulting from calcium-ceftriaxone precipitates in the lungs and kidneys, even when separate infusion lines were used.

Ringer’s Injection is contraindicated in neonates who receive ceftriaxone [see Contraindications (4), Use in Specific Populations (8.4)]. However, in patients older than 28 days, ceftriaxone and Ringer’s Injection may be administered sequentially if the infusion lines are thoroughly flushed between infusions with a compatible fluid.

5.2 Air Embolism

Cases of air embolism have been reported with pressurized administration of intravenous fluids. Air embolism may result in stroke, organ ischemia and/or infarction, and death.

Use a non-vented infusion set or close the vent on a vented set and use a dedicated line without any connections. If administration is controlled by a pumping device, care must be taken to discontinue the pumping action before the container is empty.

Pressure infusion is not recommended to increase flow rates, but if necessary, ensure all air is removed from the bag before infusion.

Refrain from applying excessive pressure (>300mmHg) causing distortion to the container such as wringing or twisting. Such handling could result in breakage of the container [see Dosage and Administration (2.2)].

5.3 Hypersensitivity Reactions

Hypersensitivity reactions, including anaphylaxis and angioedema, have been reported with Ringer’s Injection. Stop the Ringer’s Injection infusion immediately and treat patient accordingly if signs or symptoms of a hypersensitivity reaction develop. Initiate appropriate treatment as clinically indicated.

5.4 Potassium Imbalances

Hyperkalemia
Potassium-containing solutions, including Ringer’s Injection, may increase the risk of hyperkalemia. This risk is increased in patients predisposed to hyperkalemia including those with severe renal impairment, acute dehydration, extensive tissue injury or burns, heart failure, or in those using concomitant drugs that are associated with hyperkalemia.

Avoid use of Ringer’s Injection in patients with, or at increased risk for, hyperkalemia. If use cannot be avoided in these patients, closely monitor serum potassium concentrations.

Hypokalemia
The potassium concentration in Ringer’s Injection is similar to the concentration in plasma. It is insufficient to normalize the serum potassium in patients with severe hypokalemia.

5.5 Hyponatremia

Ringer’s Injection may cause hyponatremia. Hyponatremia can lead to acute hyponatremic encephalopathy characterized by headache, nausea, seizures, lethargy and vomiting. The risk of hospital-acquired hyponatremia is increased in younger pediatric patients, geriatric patients, patients treated with diuretics, and patients with cardiac or pulmonary failure or with the syndrome of inappropriate antidiuretic hormone (SIADH) (e.g., postoperative patients, patients concomitantly treated with arginine vasopressin analogs or certain antiepileptic, psychotropic, or cytotoxic drugs) [see Drug Interactions (7.1), Use in Specific Populations (8.4)].

Avoid Ringer’s Injection in patients with or at risk for hyponatremia. If use cannot be avoided in these patients, closely monitor serum sodium concentrations.

Rapid correction of hyponatremia may result in serious neurologic complications such as osmotic demyelination syndrome (ODS). To avoid complications, monitor serum sodium and chloride concentrations, fluid status, acid-base balance, and neurologic status.

5.6 Hypercalcemia

Ringer’s Injection contains calcium salts and may cause hypercalcemia. Avoid administration of Ringer’s Injection in patients with hypercalcemia, those with calcium-containing renal calculi or history of such calculi, those with conditions predisposing to hypercalcemia, or those treated with concomitant thiazide diuretics or vitamin D.

5.7 Fluid Overload

Depending on the administered volume and the infusion rate, administration of Ringer’s Injection can cause fluid overload, including pulmonary edema.

Avoid Ringer’s Injection in patients at risk for fluid and/or solute overload including patients with severe renal impairment. If use cannot be avoided in these patients, monitor fluid balance, electrolyte concentrations and acid base balance, especially during prolonged use.

6 ADVERSE REACTIONS

The following serious adverse reactions are discussed in greater detail in other sections of the labeling:

- Serious Risk with Concomitant Use with Ceftriaxone [see Warnings and Precautions (5.1)]
- Air Embolism [see Warnings and Precautions (5.2)]
- Hypersensitivity Reactions [see Warnings and Precautions (5.3)]
- Potassium Imbalances [see Warnings and Precautions (5.4)]
- Hyponatremia [see Warnings and Precautions (5.5)]
- Hypercalcemia [see Warnings and Precautions (5.6)]
- Fluid Overload [see Warnings and Precautions (5.7)]

The following adverse reactions have been identified during postapproval use of Ringer’s Products. Because these reactions are reported voluntarily from a population of uncertain size, it is not always possible to reliably estimate their frequency or establish a causal relationship to drug exposure:

General Disorders and Administration Site Conditions:
Phlebitis, extravasation, infusion site inflammation, infusion site swelling, infusion site rash, infusion site pruritus, infusion site erythema, infusion site pain, infusion site burning, and infusion site hypoaesthesia.

Hypersensitivity Reactions and Infusion Reactions:
Angioedema, chest pain/discomfort, bradycardia or tachycardia, hypotension, respiratory distress, bronchospasm, dyspnea, cough, urticaria, rash, pruritus, erythema, flushing, throat irritation, paresthesia, oral hypoesthesia, dysgeusia, nausea, anxiety, pyrexia, headache, laryngeal edema, sneezing, and injection site infection.

Metabolism and Nutrition Disorders:
Hyperkalemia, hyponatremia, and hypervolemia.

Nervous System Disorders:
Hyponatremic encephalopathy.

7 DRUG INTERACTIONS

7.1 Drugs that Affect Electrolyte and/or Fluid Balance

Hyperkalemia
Administration of Ringer’s Injection to patients concomitantly treated or recently treated with drugs that are associated with hyperkalemia increases the risk of severe and potentially fatal hyperkalemia, especially in the presence of other hyperkalemia risk factors. Avoid use of Ringer’s Injection in patients receiving drugs that are associated with hyperkalemia (e.g., potassium-sparing diuretics, ACE inhibitors, angiotensin II receptor antagonists, or calcineurin inhibitors). If concomitant use cannot be avoided, closely monitor serum potassium concentrations during concomitant use [see Warnings and Precautions (5.4)].

Hyponatremia
Administration of Ringer’s Injection to patients treated concomitantly with drugs associated with hyponatremia may increase the risk of developing hyponatremia. These drugs include diuretics and those that cause SIADH (e.g., arginine vasopressin analogs, certain antiepileptic, psychotropic, or cytotoxic drugs). Avoid use of Ringer’s Injection in patients receiving such drugs. If use cannot be avoided, closely monitor serum sodium concentrations during concomitant use [see Warnings and Precautions (5.5)].

Hypercalcemia
Avoid the use of Ringer’s Injection in patients treated with thiazide diuretics or vitamin D because these drugs can increase the risk of hypercalcemia. If use cannot be avoided, closely monitor serum calcium concentrations during concomitant use [see Warnings and Precautions (5.6)].

Hypernatremia and Fluid Retention
Administration of Ringer’s Injection to patients treated concomitantly with drugs associated with sodium and fluid retention (e.g., corticosteroids or corticotropin) may increase the risk of hypernatremia and volume overload. Avoid use of Ringer’s Injection in patients receiving such drugs. If use cannot be avoided, closely monitor serum electrolytes, fluid balance, and acid-base balance during concomitant use.

7.2 Lithium

Renal sodium and lithium clearance may be increased during concomitant use of Ringer’s Injection and lithium and may result in decreased lithium concentrations. Avoid use of Ringer’s Injection in patients receiving lithium. If use cannot be avoided, increase the frequency of monitoring of serum lithium concentrations during concomitant use.

7.3 Digoxin

Administration of calcium via use of Ringer’s Injection may increase digoxin’s effects and lead to digoxin toxicity including serious or fatal cardiac arrhythmias. In digoxin-treated patients, consider reducing the volume and/or rate of Ringer’s Injection administration.

8 USE IN SPECIFIC POPULATIONS

8.1 Pregnancy

Risk Summary

Exposure to Ringer’s Injection during pregnancy is not expected to cause major birth defects, miscarriage, or adverse maternal or fetal outcomes. Animal reproduction studies have not been conducted with this drug.

The background risk of major birth defects and miscarriage for the indicated population is unknown. All pregnancies have a background risk of birth defect, loss, or other adverse outcomes. In the U.S. general population, the estimated background risk of major birth defects and miscarriage in clinically recognized pregnancies is 2 to 4% and 15 to 20%, respectively.

8.2 Lactation

Risk Summary
The use of Ringer’s Injection is not expected to cause harm to a breastfed infant. There are no data on the presence of Ringer’s Injection in human milk, the effects on the breastfed infant, or the effects on milk production. The developmental and health benefits of breastfeeding should be considered along with the mother’s clinical need for Ringer’s Injection and any potential adverse effects on the breastfed infant from Ringer’s Injection or from the underlying maternal condition.

8.4 Pediatric Use

Ringer’s Injection is contraindicated in neonates (28 days of age or younger) who are receiving ceftriaxone due to reported deaths that occurred when neonates received ceftriaxone and intravenous calcium-containing solutions concomitantly [see Warnings and Precautions (5.1)].

The safety and effectiveness of Ringer’s Injection for use as a source of water and electrolytes have been established in pediatric patients of all ages, including neonates.

Closely monitor plasma electrolyte concentrations in young pediatric patients with immature kidney function who may have decreased ability to maintain fluid and electrolyte balance [see Warnings and Precautions (5.4, 5.5, 5.6, 5.7)].

8.5 Geriatric Use

Geriatric patients treated with Ringer’s Injection are at increased risk of developing electrolyte imbalances. Ringer’s Injection is substantially excreted by the kidney, and the risk of adverse reactions to Ringer’s Injection may be greater in patients with renal impairment than in patients with normal renal function. Because geriatric patients are more likely to have decreased renal function, consider monitoring renal function in geriatric patients and consider starting the infusion at the low end of the dosing range.

8.6 Renal Impairment

Administration of Ringer’s Injection to patients with or at risk of severe renal impairment, may result in hyperkalemia and/or fluid overload [see Warnings and Precautions (5.4, 5.7)]. Avoid Ringer’s Injection in patients with severe renal impairment. If use cannot be avoided in such patients, monitor for development of these adverse reactions.

10 OVERDOSAGE

Excessive administration of Ringer’s Injection can cause:

- Hyperkalemia and hypernatremia, especially in patients with severe renal impairment.
- Fluid overload (which can lead to pulmonary and/or peripheral edema).
- Hypercalcemia

Overdose interventions include Ringer’s Injection discontinuation, treatment of electrolyte imbalances, and close monitoring of fluid balance and electrolyte concentrations [see Warnings and Precautions (5.4, 5.5, 5.6, 5.7)].

11 DESCRIPTION

Ringer’s Injection USP is a sterile, nonpyrogenic solution for fluid and electrolyte replenishment in a single-dose container for intravenous administration.

Composition, osmolarity, pH, ionic concentration and caloric content are shown in Table 1.

Table 1

 | Size (mL) | Composition (g/L) |  |  | Osmolarity [Normal physiologic osmolarity range is approximately 280 to 310 mOsmol/L.] (mOsmol/L) (calc) | pH | Ionic Concentration (mEq/L) |  |  |  | Caloric Content (kcal/L)
 | Size (mL) | Sodium Chloride, USP | Calcium Chloride, USP | Potassium Chloride, USP | Osmolarity [Normal physiologic osmolarity range is approximately 280 to 310 mOsmol/L.] (mOsmol/L) (calc) | pH | Sodium | Potassium | Calcium | Chloride | Caloric Content (kcal/L)
Ringer’s Injection, USP | 1000 | 8.6 | 0.33 | 0.3 | 310 | 5.8; (5.0 to; 7.5) | 147 | 4 | 4.5 | 156 | 0

The chemical name, structural formula, and molecular weight of the active ingredients are shown in Table 2.

Table 2

Ingredients | Molecular Formula | Molecular Weight
Sodium Chloride USP |  | 58.44
Potassium Chloride USP |  | 74.55
Calcium Chloride Dihydrate USP |  | 147.02

Not made with natural rubber latex, PVC or DEHP.

The plastic container is made from a multilayered film developed for parenteral drugs. It contains no plasticizers and has minimal leachables. The solution contact layer is a rubberized copolymer of ethylene and propylene. The container-solution unit is a closed system and is not dependent upon entry of external air during administration. The container is overwrapped to provide protection from the physical environment and to provide an additional moisture barrier when necessary.

The closure system has two ports; the one for the administration set has a tamper evident plastic protector and the other is a medication addition site [see Dosage and Administration (2.3)].

12 CLINICAL PHARMACOLOGY

12.1 Mechanism of Action

Ringer’s Injection is a source of water, and electrolytes.

- Sodium, the major cation of the extracellular fluid, functions primarily in the control of water distribution, fluid balance, and osmotic pressure of body fluids. Sodium is also associated with chloride and bicarbonate in the regulation of the acid-base equilibrium of body fluid.
- Potassium, the principal cation of intracellular fluid, participates in carbohydrate utilization and protein synthesis and is critical in the regulation of nerve conduction and muscle contraction, particularly in the heart.
- Chloride, the major extracellular anion, closely follows the metabolism of sodium, and changes in the acid-base balance of the body are reflected by changes in the chloride concentration.
- Calcium, an important cation, provides the framework of bones and teeth in the form of calcium phosphate and calcium carbonate. In the ionized form, calcium is essential for the functional mechanism of the clotting of blood, normal cardiac function, and regulation of neuromuscular irritability.

12.2 Pharmacodynamics

The exposure-response relationship and time course of pharmacodynamic response for the safety and effectiveness of Ringer’s Injection have not been fully characterized.

12.3 Pharmacokinetics

Elimination
Metabolism/Excretion
Potassium: Normally about 80 to 90% of the potassium intake is excreted in the urine; the remainder is excreted in feces and to a smaller extent, in perspiration.

Sodium and Chloride: The distribution and excretion of sodium (Na^+) and chloride (Cl^−) are largely under the control of the kidney which maintains a balance between intake and output.

13 NONCLINICAL TOXICOLOGY

13.1 Carcinogenesis, Mutagenesis, Impairment of Fertility

Carcinogenicity, genetic toxicology, and animal fertility studies have not been conducted with Ringer’s Injection.

16 HOW SUPPLIED/STORAGE AND HANDLING

How Supplied
Ringer’s Injection USP is supplied sterile and nonpyrogenic in single-dose EXCEL® Containers packaged 12 per case.

It is available in the following presentation:

NDC | REF | Size
0264-7780-00 | L7800 | 1000 mL

Canada DIN 01936034

Storage and Handling
Store at 20°C to 25°C (68°F to 77°F); excursions permitted between 15°C to 30°C (59°F to 86°F). [See USP Controlled Room Temperature.]

Minimize exposure of Ringer’s Injection USP to heat. Avoid excessive heat. Protect from freezing.

EXCEL is a registered trademark of B. Braun Medical Inc.

Rx only

B. Braun Medical Inc.
Bethlehem, PA 18018-3524 USA
1-800-227-2862

In Canada, distributed by:
B. Braun of Canada, Ltd.
Scarborough, Ontario M1H 2W4

Y36-003-098 LD-497-4

PRINCIPAL DISPLAY PANEL

Ringer's
Injection USP
REF L7800
NDC 0264-7780-00
DIN 01936034
HK 22699
1000 mL
EXCEL® CONTAINER

Each 100 mL contains: Sodium Chloride USP 0.86 g;
Calcium Chloride•2H2O USP 0.033 g;
Potassium Chloride USP 0.03 g; Water for Injection USP qs

pH: 5.8 (5.0-7.5); Calc. Osmolarity: 310 mOsmol/liter

Electrolytes (mEq/liter):
Na^+ 147; K^+ 4; Ca^++ 4.5; Cl^- 156

Sterile, nonpyrogenic. Single dose container. Do not use in series connection.
For intravenous use only. Use only if solution is clear and container and seals
are intact.

WARNINGS: Do Not Administer Simultaneously With Blood. Some additives
may be incompatible. Consult with pharmacist. When introducing additives,
use aseptic techniques. Mix thoroughly. Do not store.

Recommended Storage: Room temperature (25°C). Avoid excessive heat.
Protect from freezing. See Package Insert.

Do not remove overwrap until ready for use. After removing the overwrap,
check for minute leaks by squeezing container firmly. If leaks are found,
discard solution as sterility may be impaired.

Not made with natural rubber latex, PVC or DEHP.
Rx only
EXCEL is a registered trademark of B. Braun Medical Inc.

B. Braun Medical Inc.
Bethlehem, PA 18018-3524 USA
1-800-227-2862
www.bbraun.com

In Canada, distributed by:
B. Braun of Canada, Ltd.
Scarborough, Ontario M1H 2W4

Y94-003-233 LD-139-3

EXP
LOT